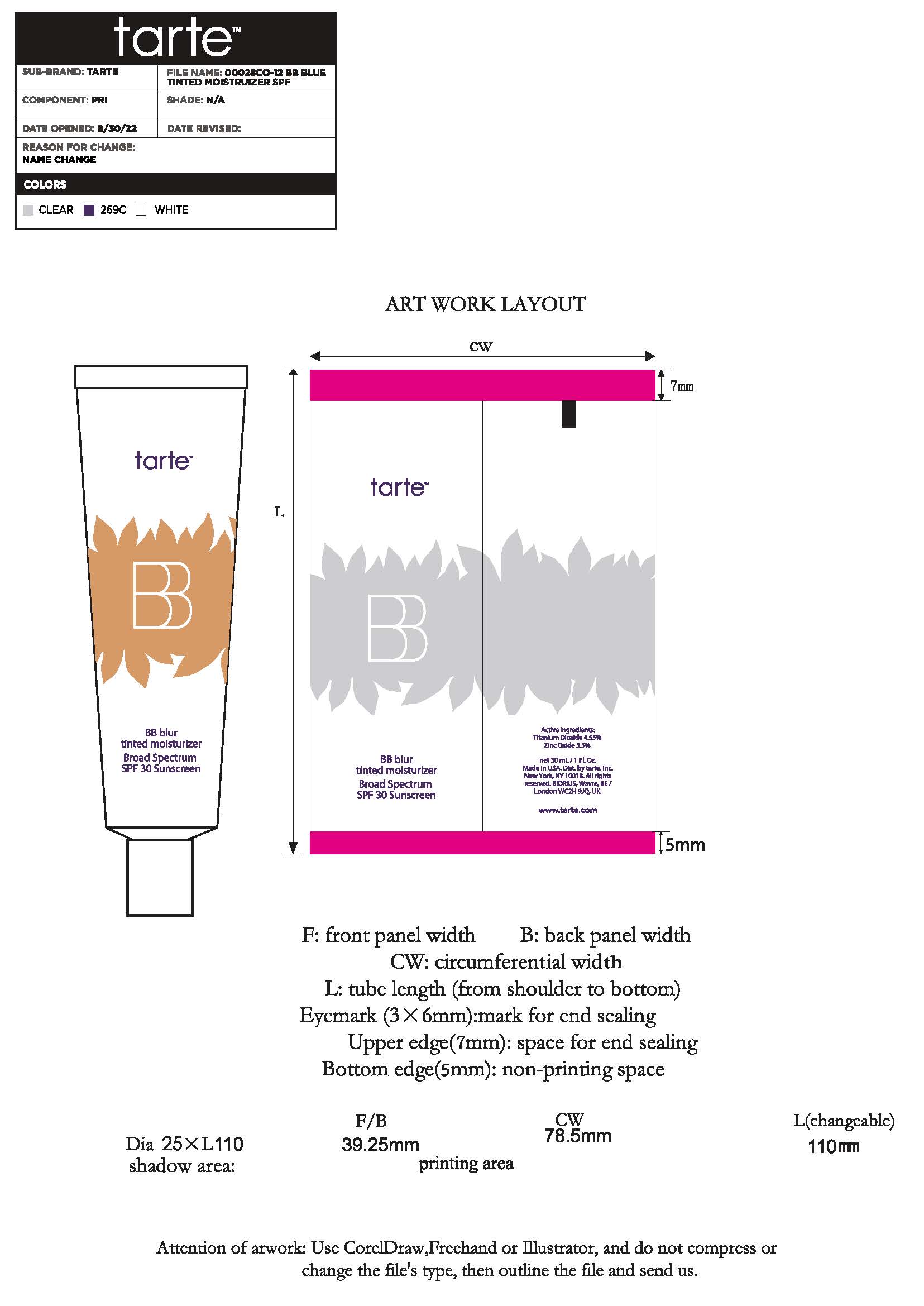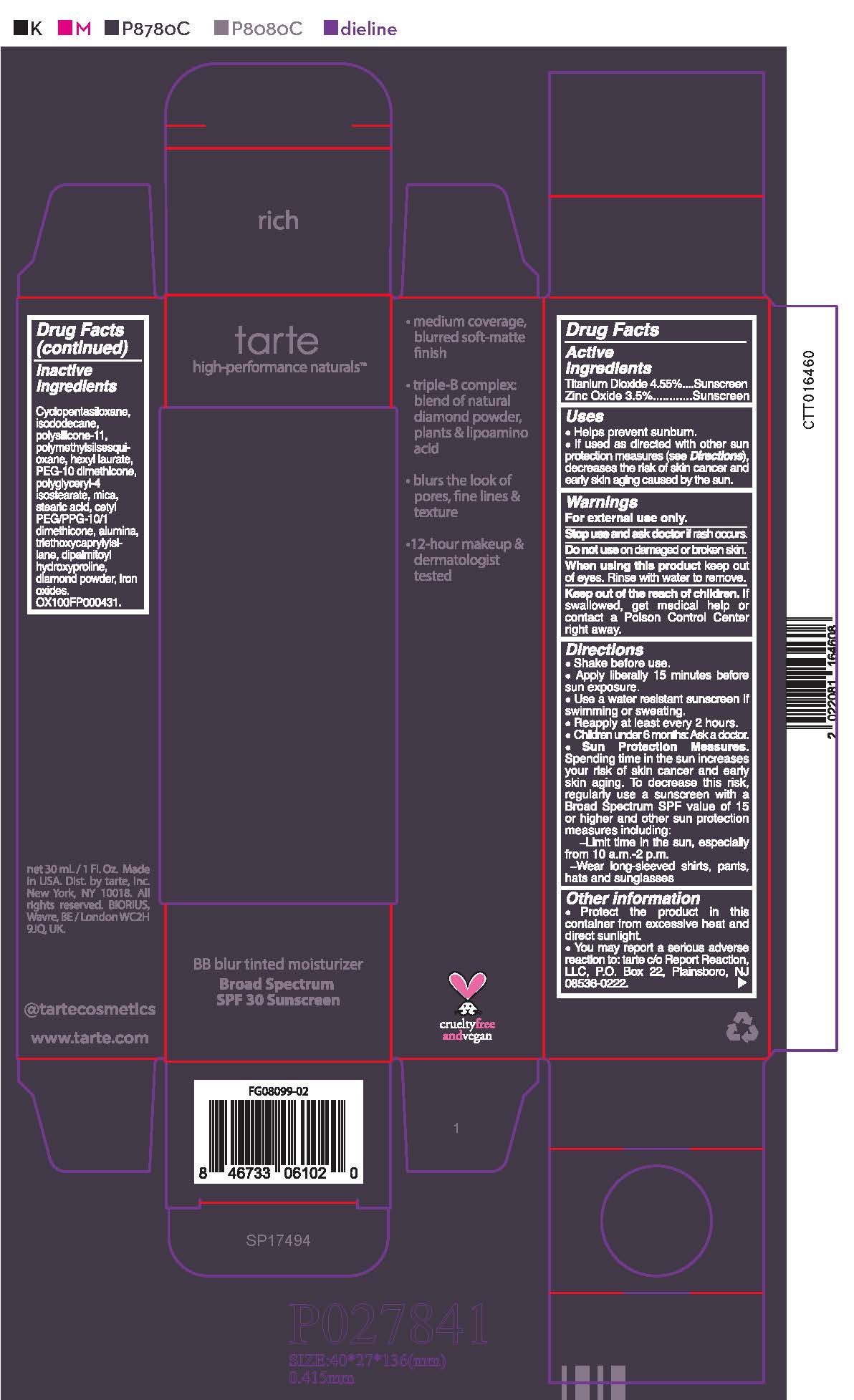 DRUG LABEL: Cream
NDC: 61354-101 | Form: CREAM
Manufacturer: Oxygen Development LLC
Category: otc | Type: HUMAN OTC DRUG LABEL
Date: 20230627

ACTIVE INGREDIENTS: TITANIUM DIOXIDE 4.54 mg/100 mg; ZINC OXIDE 3.498 mg/100 mg
INACTIVE INGREDIENTS: ISODODECANE 10.69 mg/100 mg; HEXYL LAURATE 1.76 mg/100 mg; DIMETHICONE/VINYL DIMETHICONE CROSSPOLYMER (SOFT PARTICLE) 4.68 mg/100 mg; POLYMETHYLSILSESQUIOXANE (4.5 MICRONS) 3.19 mg/100 mg; PEG-10 DIMETHICONE (220 CST) 1.65 mg/100 mg; CYCLOMETHICONE 5 55.74 mg/100 mg; POLYGLYCERYL-4 ISOSTEARATE 1.5 mg/100 mg

tarte BB blur tinted moisturizer Broad Spectrum SPF 30 Sunscreen

Active ingredient

Titanium Dioxide 4.55%

Zinc Oxide 3.5%

Purpose

Sunscreen

Uses

Helps prevent sunburn. If used as directed with other sun protection measures (see directions), decreases the risk of skin cancer and early aging caused by the sun.

Warnings

For external use only. Stop use and ask a doctor if rash occurs. Do not use on damage or broken skin.

When using

When using this product keep out of eyes. Rinse with water to remove.

Keep out of the reach of children.

If swallowed, get medical help or contact a Poison Control center right away.

Directions

Shake before use. Apply liberally 15 minutes before sun exposure. Use a water resistant sunscreen if swimming or sweating. Reapply at least every 2 hours. Children under 6 months: Ask a doctor. Sun protection measures. Spending time in the sun increases your risk of skin cancer and early skin aging. To decrease the risk, regularly use a sunscreen with a Broad Spectrum SPF value of 15 or higher and other sun protection measures including:

- Limit time in the sun, especially from 10 a.m. - 2 p.m.

- Wear long-sleeved shirts, pants, hats, and sunglasses

Other information

Protect the product in this container from excessive heat and direct sunlight.

You may report a serious adverse reaction to: tarte c/o Report Reaction, LLC, P.O. Box 22, Plainsboro, NJ 08536-0222

Inactive Ingredient

Cyclopentasiloxane, Isododecane, Polysilicone-11, Polymethylsilsesquioxane, Hexyl Laurate, PEG-10 Dimethicone, Polyglyceryl-4 Isostearate, Stearic Acid, Cetyl PEG/PPG-10/1 Dimethicone, Alumina, Triethoxycaprylylsilane, Dipalmitoyl Hydroxyproline, Diamond Powder